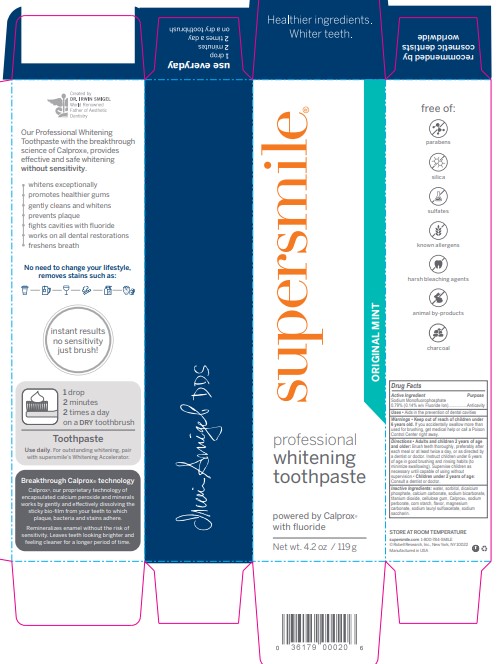 DRUG LABEL: Supersmile
NDC: 53567-0030 | Form: PASTE, DENTIFRICE
Manufacturer: Robell Research, Inc
Category: otc | Type: HUMAN OTC DRUG LABEL
Date: 20260128

ACTIVE INGREDIENTS: SODIUM MONOFLUOROPHOSPHATE 0.14 g/100 g
INACTIVE INGREDIENTS: STARCH, CORN; CARBOXYMETHYLCELLULOSE SODIUM; SACCHARIN SODIUM; CALCIUM PEROXIDE; WATER; SODIUM PERBORATE TETRAHYDRATE; CALCIUM CARBONATE; TITANIUM DIOXIDE; DIBASIC CALCIUM PHOSPHATE DIHYDRATE; MAGNESIUM CARBONATE; SODIUM LAURYL SULFOACETATE; SORBITOL; SODIUM BICARBONATE

5890109 Supersmile Professional Whitening Toothpaste Original Mint (86-60110)

ACTIVE INGREDIENT

Sodium Monoflurophosphate 0.79% (0.14% w/v Fluoride Ion) .................... Anticavity

INACTIVE INGREDIENT

Water, Sorbitol, Dicalcium Phosphate, Calcium Carbonate, Sodium Bicarbonate, Titanium Dioxide, Cellulose Gum, Calprox®, Sodium Perborate, Corn Starch, Flavor, Magnesium Carbonate, Sodium Lauryl Sulfoacetate, Sodium Saccharin

PURPOSE

Aids in the prevention of dental cavities

Keep out of reach of children under 6 years old. If you accedentally swallow more than used for brushing, get medical help or call a Posion control center rigth away.

Keep out of reach of children under 6 years old. If you accidentally swallow more than used for brushing, get medical help or call a Posion control center rigth away.

INDICATIONS AND USAGE

Place a pearl-sized drop of Whitening toothpaste on a dry toothbrush and brush in a circular motion for 2 minutes, 2x a day.

DOSAGE AND ADMINISTRATION

Adults and children 2 years of age and older: Brush teeth thoroughly, preferably after each meal or at least twice a day, or as directed by a dentist or doctor. Instruc children under 6 years of age in good brushing and rinsing habots (to minimize swallowing). Supervise children as necessary until capable of using wihtout supervision.

Children under 2 years of age: Consult a dentist or doctor.